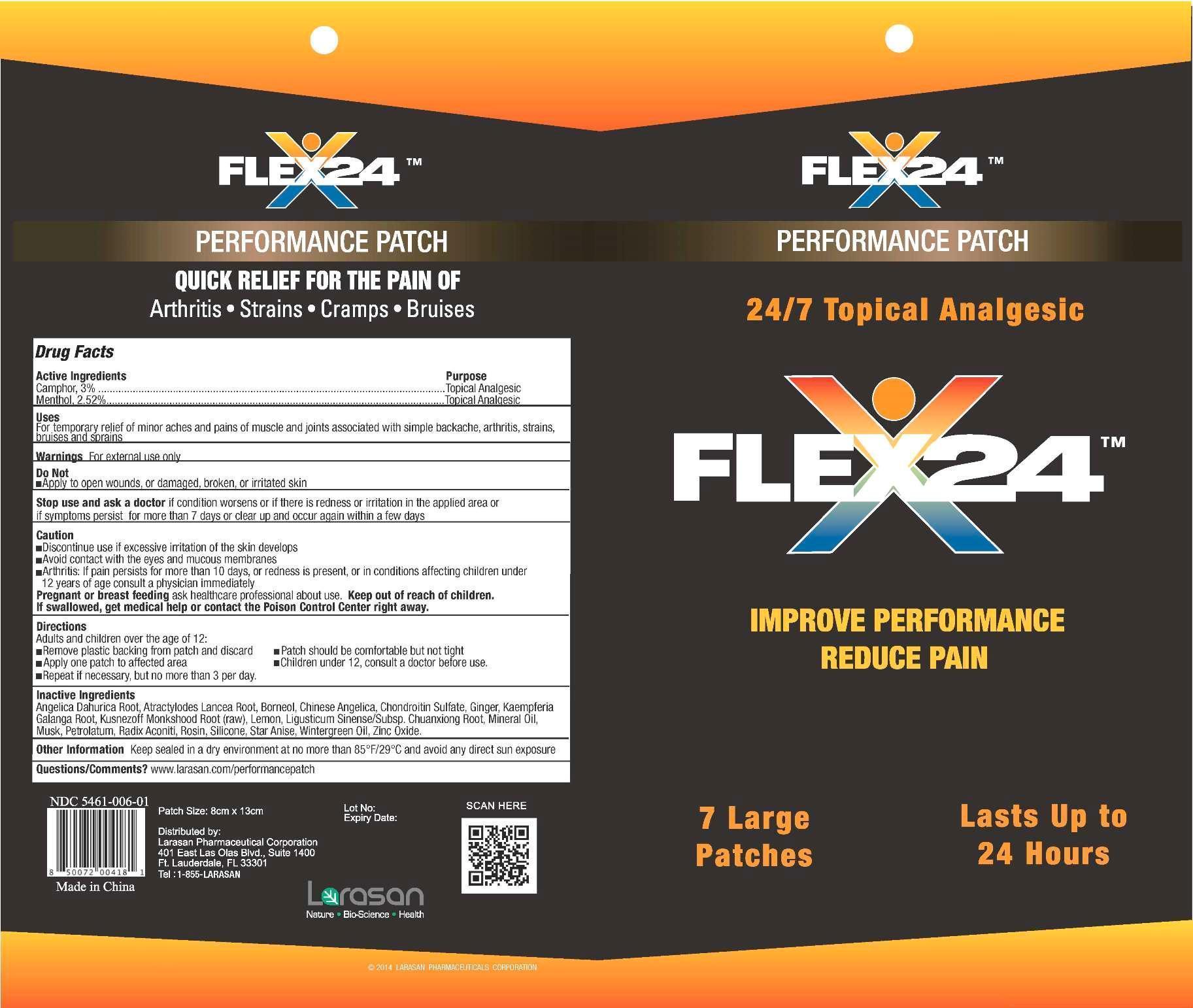 DRUG LABEL: Flex24 Performance
NDC: 54641-006 | Form: PATCH
Manufacturer: Larasan Pharmaceutical Corporation
Category: otc | Type: HUMAN OTC DRUG LABEL
Date: 20191208

ACTIVE INGREDIENTS: CAMPHOR (NATURAL) 3 g/100 g; MENTHOL 2.52 g/100 g
INACTIVE INGREDIENTS: ANGELICA DAHURICA ROOT; ATRACTYLODES LANCEA ROOT; BORNEOL; ANGELICA SINENSIS ROOT; CHONDROITIN SULFATE (BOVINE); GINGER; KAEMPFERIA GALANGA ROOT; ACONITUM KUSNEZOFFII ROOT; Lemon; LIGUSTICUM SINENSE SUBSP. CHUANXIONG ROOT; MINERAL OIL; MOSCHUS BEREZOVSKII MUSK SAC RESIN; PETROLATUM; ACONITUM NAPELLUS ROOT; ROSIN; STAR ANISE; METHYL SALICYLATE; ZINC OXIDE

Active Ingredients

Camphor, 3%

Menthol, 2.52%

Purpose

Topical analgesic

Uses

For temporary relief of minor aches and pains of muscle and joints associated with simple arthritis, strains, bruises and sprains

Warnings

For external use only

Do not

apply to open wounds, or damaged, broken, or irritated skin

Stop use and ask a doctor

if condition worsens or if there is redness or irritation in the applied area or if symptoms persist for more than 7 days or clear up and occur again within a few days

Caution

- Discontinue use if excessive irritation of the skin develops
- Avoid contact with the eyes and mucous membranes
- Arthritis: If pain persists for more than 10 days, or redness is present, or in conditions affecting children under 12 years of age consult a physician immediately

Pregnancy or breast feeding

ask healthcare professional about use

Keep out of reach of children

If swallowed, get medical help or contact the Poison Control Center right away

Directions

Adults and children over the age of 12:

• Remove plastic backing from patch and discard

• Apply one patch to affected area

•Patch should be comfortable but not tight

• Repeat if necessary but no more than 3 per day

Children under 12, consult a doctor before use.

Inactive Ingredients

Angelica Dahurica Root, Atractylodes Lancea Root, Borneol, Chinese Angelica, Chondroitin Sulfate, Ginger, Kaempferia Galanga Root, Kusnezoff Monkshood Root (raw), Lemon, Ligusticum Sinense/Subsp. Chuanxiong Root, Mineral Oil, Musk, Petrolatum, Radix Aconiti, Rosin, Silicone, Star Anise, Wintergreen Oil, Zinc Oxide

Other Information

Keep sealed in a dry environment at no more than 85°F/29°C and avoid any direct sun exposure

Questions/Comments?

www.larasan.com/performancepatch

Flex24™ Performance Patch

Quick Relief for the Pain Of

Arthritis • Strains • Cramps • Bruises

Distributed By

Larasan Pharmaceutical Corporation

401 East Las Olas Blvd., Suite 1400

Ft. Lauderdale, FL 33301

Tel. 1-855-LARASAN

NDC 54641-006-01

Made in China

Patch size 8 cm x 13 cm

PACKAGE LABEL

Flex24™ Performance Patch
24/7 Topical Analgesic
Improve Performance
Reduce Pain
7 Large Patches
Lasts Up to 24 Hours